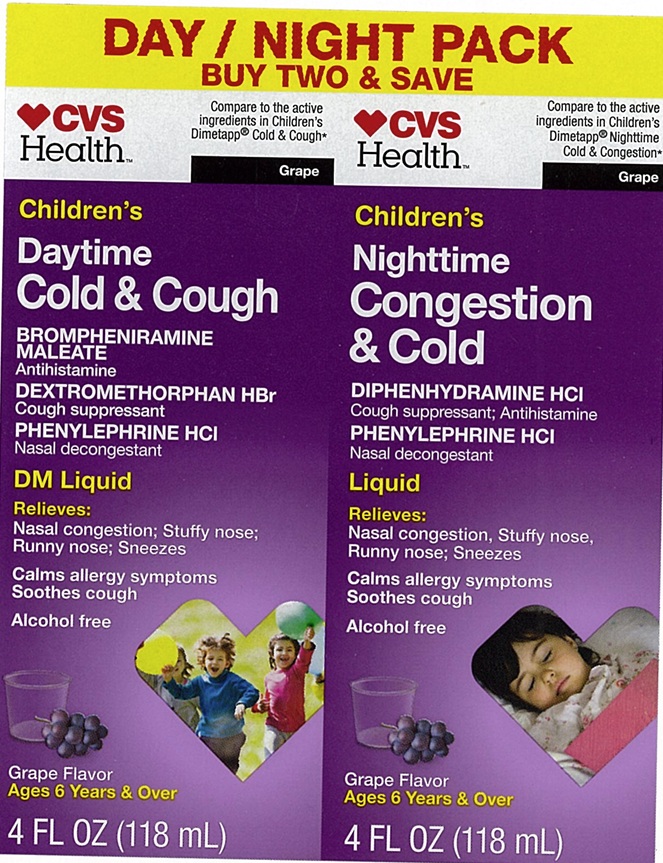 DRUG LABEL: Daytime Cold and Cough Nighttime Cold and Congestion
NDC: 51316-939 | Form: KIT | Route: ORAL
Manufacturer: CVS
Category: otc | Type: Human OTC Drug Label
Date: 20250203

ACTIVE INGREDIENTS: BROMPHENIRAMINE MALEATE 1 mg/5 mL; DEXTROMETHORPHAN HYDROBROMIDE 5 mg/5 mL; PHENYLEPHRINE HYDROCHLORIDE 2.5 mg/5 mL; DIPHENHYDRAMINE HYDROCHLORIDE 6.25 mg/5 mL; PHENYLEPHRINE HYDROCHLORIDE 2.5 mg/5 mL
INACTIVE INGREDIENTS: ANHYDROUS CITRIC ACID; FD&C BLUE NO. 1; FD&C RED NO. 40; GLYCERIN; PROPYL GALLATE; PROPYLENE GLYCOL; WATER; SORBITOL; SUCRALOSE; SODIUM BENZOATE; SODIUM CITRATE, UNSPECIFIED FORM; ANHYDROUS CITRIC ACID; FD&C BLUE NO. 1; FD&C RED NO. 40; GLYCERIN; PROPYLENE GLYCOL; PROPYL GALLATE; WATER; SODIUM BENZOATE; SODIUM CITRATE; SORBITOL; SUCRALOSE

Children's Daytime Cold & Cough Nighttime Congestion and Cold

ACTIVE INGREDIENT(S) FOR DAYTIME (in each 5 mL)

Brompheniramine Maleate 1 mg

Dextromethorphan HBr 5 mg

Phenylephrine HCI 2.5 mg

ACTIVE INGREDIENT(S) FOR NIGHTTIME (in each 5 mL)

Diphenhydramine HCI 6.25 mg

Phenylephrine HCI 2.5 mg

PURPOSE FOR DAYTIME

Antihistamine

Cough suppressant

Nasal decongestant

PURPOSE FOR NIGHTTIME

Antihistamine / Cough suppressant

Nasal Decongestant

USE(S)

DAYTIME

- temporarily relieves cough due to minor
  bronchial irritation as may occur with a cold, and
  nasal congestion due to the common cold, hay
  fever or other upper respiratory allergies
- temporarily relieves these symptoms due to hay
  fever (allergic rhinitis): • sneezing • itching of the
  nose or throat • runny nose • itchy, watery eyes
- temporarily restores freer breathing through the nose

NIGHTTIME

- tempuradly relieves these symptoms occuring with
  a cold, hay fever or other upper respiratory allergies:
  • sneezing. itching of the nose or throat. runny nose
  • itchy, watery eyes. cough. nasal congestion

WARNINGS

.

DO NOT USE

Daytime

Do not use

- to sedate a child or to make a child sleepy

- if you are now taking a prescription monoamine oxidase inhibitor (MAOI) (certain drugs for depression, psychiatric, or emotional conditions, or Parkinson’s disease), or for 2 weeks after stopping the MAOI drug. If you do not know if your prescription drug contains an MAOI, ask a doctor or pharmacist before taking this product.

Nighttime

Do not use

- to sedate a child or to make a child sleepy
- if you are now taking a prescription monoamine oxidase inhibitor (MAOI) (certain drugs for depression, psychiatric, or emotional conditions, or Parkinson’s disease), or for 2 weeks after stopping the MAOI drug. If you do nut know if your prescription drug contains an MAOI, ask a doctor
  or pharmacist before taking this product.
- with any other product containing diphenhydramine, even one used on skin

ASK A DOCTOR BEFORE USE IF YOU HAVE

DAYTIME

- heart disease
- glaucoma
- diabetes
- thyroid disease
- high blood pressure
- difficulty in urination due to an enlarged prostate gland
- cough that occurs wilt too much phlegm (mucus)
- a breathing problem or persistent or chronic cough that lasts such as occurs with smoking, asthma, chronic bronchitis or emphysema

NIGHTTIME

- heart disease
- glaucoma
- diabetes
- thyroid disease
- high blood pressure
- difficulty in urination due to an enlarged prostate gland
- cough that occurs with too much phlegm (mucus)
- a breathing problem or chronic cough that lasts or as occurs with smoking, asthma, chronic bronchitis or emphysema

ASK A DOCTOR OR PHARMACIST BEFORE USE IF YOU ARE

DAYTIME

- taking any other oral nasal decongestant or stimulant
- taking sedatives or tranquilizers

NIGHTTIME

- taking any other oral nasal decongestant or stimulant
- taking sedatives or tranquilizers

WHEN USING THIS PRODUCT

DAYTIME

- do not take more than directed
- may cause drowsiness
- alcohol, sedatives, and tranquilizers may increase drowsiness
- avoid alcoholic beverages
- be careful when driving a motor vehicle or operating machinery
- excitability may occur, especially in children

NIGHTTIME

- do not take more than directed
- may cause drowsiness
- alcohol, sedatives, and tranquilizers may increase drowsiness
- avoid alcoholic beverages
- be careful when driving a motor vehicle or operating machinery
- excitability may occur, especially in children

STOP USE AND ASK DOCTOR IF

- nervousness, dizziness or sleeplessness occur
- symptoms do not improve within 7 days or are accompanied by fever
- cough lasts more than 7 days, comes back, or is accompanied by fever, rash, or persistent headache. These could be signs of a serious
  condition.

IF PREGNANT OR BREAST-FEEDING

ask a health professional before use.

KEEP OUT OF REACH OF CHILDREN

In case of overdose, get medical help or contact a Poison Control Center right away.

DIRECTIONS

DAYTIME

- do not take more than 6 doses in any 24-hour period
- do not exceed recommended dosage
- mL milliliter
- tsp = teaspoon

Age | Dose
adults & children 12 years over | 4 tsp (20 mL) every 4 hours
children 6 years to under 12 years | 2 tsp (10 mL) every 4 hours
children under 6 years | do not use

NIGHTTIME

- do not take more than 6 doses in any 24-hour period
- do not exceed recommended dosage
- mL milliliter
- tsp = teaspoon

Age | Dose
adults & children 12 years over | 4 tsp (20 mL) every 4 hours
children 6 years to under 12 years | 2 tsp (10 mL) every 4 hours
children under 6 years | do not use

OTHER INFORMATION

DAYTIME

- each teaspoon (tsp) contains: sodium 5 mg
- store at 20-25ºC (68-77ºF)
- measuring cup provided

NIGHTTIME

- each teaspoon (tsp) contains: sodium 5 mg
- store at 20-25ºC (68-77ºF)
- measuring cup provided

INACTIVE INGREDIENTS

DAYTIME

anhydrous citric acid, artificial flavor, FD&C blue #1, FD&C red #40, glycerin, propylene glycol, propyl gallate, purified water, sodium benzoate, sodium citrate, sorbitol, sucralose
NIGHTTIME
anhydrous citric acid, artificial flavor, FD&C blue #1, FD&C red #40, glycerin, propylene glycol, propyl gallate, purified water, sodium benzoate, sodium citrate, sorbitol, sucralose

PRINCIPAL DISPLAY PANEL

DAY/NIGHT PACK

NDC 51316-939-04

CVS Health

Compare to the active Ingredients in Children's Dimetapp® Cold & Cough*

Compare to the active Ingredients in Children's Dimetapp® Nighttime Cold & Cough*

Children's Daytime Cold & Cough

BROMPHENIRAMINE MALEATE
Antihistamine

DEXTROMETHORPHAN HBr

Cough suppressant

PHENYLEPHRINE HCl

Nasal decongestant

DM Liquid

Relieves:

Nasal congestion; Stuffy nose;

Runny nose; Sneezes

Calms allergy symptoms
Soothes Cough

Alcohol Free

Grape Flavor

Ages 6 Years & Over

4 FL OZ (118 mL)

Children's Nighttime Congestion & Cold

DIPHENYLHYDRAMINE HCl

Cough suppressant; Antihistamine

PHENYLEPHRINE HCl

Nasal decongestant

Liquid

Relieves:

Nasal congestion; Stuffy nose;

Runny nose; Sneezes

Calms allergy symptoms
Soothes Cough

Alcohol Free

Grape Flavor

Ages 6 Years & Over

4 FL OZ (118 mL)